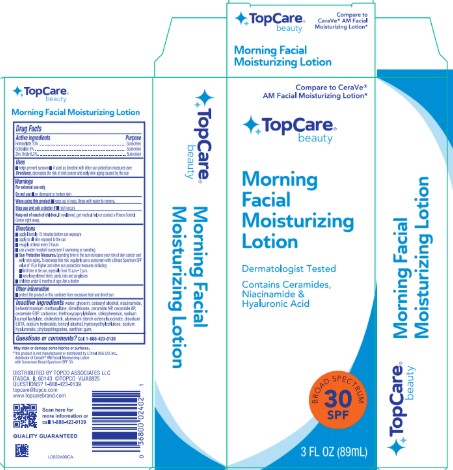 DRUG LABEL: Homosalate, Octisalate, Zinc oxide
NDC: 76162-957 | Form: LOTION
Manufacturer: Topco Associates LLC
Category: otc | Type: HUMAN OTC DRUG LABEL
Date: 20260213

ACTIVE INGREDIENTS: HOMOSALATE 100 mg/1 mL; ZINC OXIDE 63 mg/1 mL; OCTISALATE 50 mg/1 mL
INACTIVE INGREDIENTS: CETOSTEARYL ALCOHOL; CERAMIDE 1; ALUMINUM STARCH OCTENYLSUCCINATE; CHLORPHENESIN; SODIUM LAUROYL LACTYLATE; CHOLESTEROL; CERAMIDE AP; CARBOMER HOMOPOLYMER, UNSPECIFIED TYPE; HYDROXYETHYL CELLULOSE, UNSPECIFIED; HYALURONATE SODIUM; EDETATE DISODIUM; DIMETHICONE, UNSPECIFIED; WATER; BEHENTRIMONIUM METHOSULFATE; CERAMIDE NP; TRIETHOXYCAPRYLYLSILANE; XANTHAN GUM; SODIUM HYDROXIDE; NIACINAMIDE; BENZYL ALCOHOL; PHYTOSPHINGOSINE; GLYCERIN

Top Care 957.000/957AA
Facial Moisturizing Morning Sunscreen Lotion Broad Spectrum SPF 30

Claims

Top Care® beauty

Morning Facial Moisturizing Lotion

Active ingredients

Homosalate 10%

Octisalate 5%

Zinc Oxide 6.3%

Purpose

Sunscreen

Uses

- helps prevent sunburn
- if used as directed with other sun protection measures (see Directions), decreases the risk of skin cancer and early skin aging caused by the sun

Warnings

For external use only

Do not use

- on damaged or broken skin

When using this product

- keep out of eyes. Rinse with water to remove.

Stop use and ask a doctor if

- rash occurs

Keep out of reach of children.

If swallowed, get medical help or contact a Poison Control Center right away.

Directions

- apply liberally {and evenly} 15 minutes before sun exposure
- apply to all skin exposed to the sun
- reapply at least every 2 hours
- use a water resistant sunscreen if swimming or sweating
- Sun Protection Measures. Spending time in the sun increases your risk of skin cancer and early skin aging. To decrease this risk, regularly use a sunscreen with a Broad Spectrum SPF value of 15 or higher and other sun protection measures including:
- limit time in the sun, especially from 10 a.m.–2 p.m.
- wear long-sleeved shirts, pants, hats and sunglasses
- children under 6 months of age: Ask a doctor

Other information

- protect the product in this container from excessive heat and direct sun

Inactive Ingredients

water, glycerin, cetearyl alcohol, niacinamide, behentrimonium methosulfate, dimethicone, ceramide NP, ceramide AP, ceramide EOP, carbomer, triethoxycaprylylsilane, chlorphenesin, sodium lauroyl lactylate, cholesterol, aluminum starch octenylsuccinate, disodium EDTA, sodium hydroxide, benzyl alcohol, hydroxyethylcellulose, sodium hyaluronate, phytosphingosine, xanthan gum

Questions or comments?

Call 1-888-423-0139

Disclaimers

May stain or damage some fabrics or surfaces.

*This product is not manufactured or distributed by L’Oreal USA S/D, Inc., distributor of CeraVe® AM Facial Moisturizing Lotion with Sunscreen Broad Spectrum SPF 30.

Adverse Reactions

DISTRIBUTED BY TOPCO ASSOCIATES, LLC

ITASCA, IL 60143 ©TOPCO

QUESTIONS? 1-888-423-0139

topcare@topco.com

www.topcarebrand.com

Scan here for more information or call 1-888-423-0139

QUALITY GUARANTEED

Top Panel and Side Panel Claims

Top Care® beauty

Compare to CeraVe® AM Facial Moisturizing Lotion*

Morning Facial Moisturizing Lotion

Principal Display Panel

Compare to CeraVe® AM Facial Moisturizing Lotion*

Top Care® beauty

Morning Facial Moisturizing Lotion

Dermatologist Tested

Contains Ceramides, Niacinamide & Hyaluronic Acid

BROAD SPECTRUM 30 SPF

3 FL OZ (89 mL)